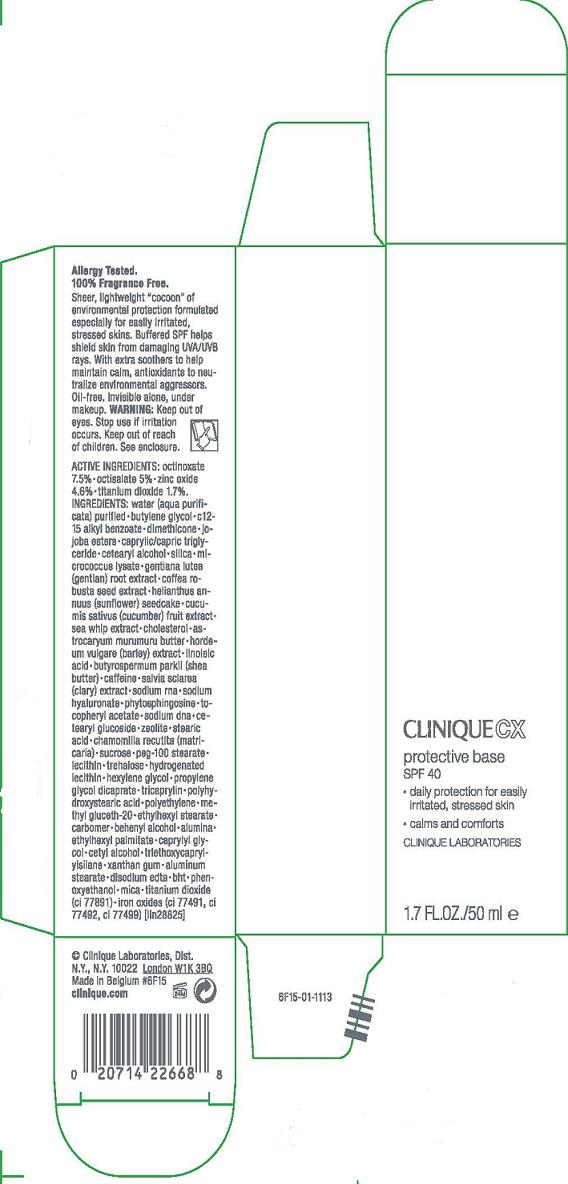 DRUG LABEL: CLINIQUE CX
NDC: 49527-953 | Form: CREAM
Manufacturer: CLINIQUE LABORATORIES INC
Category: otc | Type: HUMAN OTC DRUG LABEL
Date: 20101103

ACTIVE INGREDIENTS: OCTINOXATE 7.5 mL/100 mL; OCTISALATE 5.0 mL/100 mL; ZINC OXIDE 4.6 mL/100 mL; TITANIUM DIOXIDE 1.7 mL/100 mL
INACTIVE INGREDIENTS: BUTYLENE GLYCOL; C12-15 ALKYL BENZOATE

ACTIVE INGREDIENT

active ingredients: octinoxate 7.50% [] octisalate 5.00% [] zinc oxide 4.60% [] titanium dioxide 1.70%

INACTIVE INGREDIENT

inactive ingredients: water (aqua purificata) purified [] butylene glycol [] c12-15 alkyl benzoate [] dimethicone [] jojoba esters [] caprylic/capric triglyceride [] cetearyl alcohol [] silica [] micrococcus lysate [] gentiana lutea (gentian) root extract [] coffea robusta seed extract [] helianthus annuus (sunflower) seedcake [] cucumis sativus (cucumber) fruit extract [] sea whip extract [] cholesterol [] astrocaryum murumuru butter [] hordeum vulgare (barley) extract [] linoleic acid [] butyrospermum parkii (shea butter) [] caffeine [] salvia sclarea (clary) extract [] sodium rna [] sodium hyaluronate [] phytosphingosine [] tocopheryl acetate [] sodium dna [] cetearyl glucoside [] zeolite [] stearic acid [] chamomilla recutita (matricaria) [] sucrose [] peg-100 stearate [] lecithin [] trehalose [] hydrogenated lecithin [] hexylene glycol [] propylene glycol dicaprate [] tricaprylin [] polyhydroxystearic acid [] polyethylene [] methyl gluceth-20 [] ethylhexyl stearate [] carbomer [] behenyl alcohol [] alumina [] ethylhexyl palmitate [] caprylyl glycol [] cetyl alcohol [] triethoxycaprylylsilane [] xanthan gum [] aluminum stearate [] disodium edta [] bht [] phenoxyethanol [] mica [] titanium dioxide (ci 77891) [] iron oxides (ci 77491, ci 77492, ci 77499)

WARNINGS

warning: keep out of eyes. stop use if irritation occurs.

keep out of reach of chidren

PACKAGE LABEL

principal display panel:

CLINIQUE CX
PROTECTIVE BASE
SPF 40

- daily protection for easily stressed skin
- calms and comforts

CLINIQUE LABORATORIES
1.7 fl oz/50 ml
clinique laboratories, distr.
new york, ny
10022
clinique.com